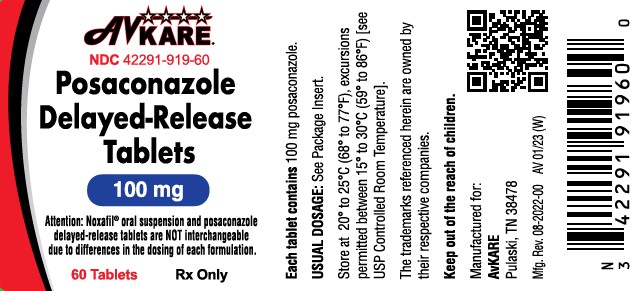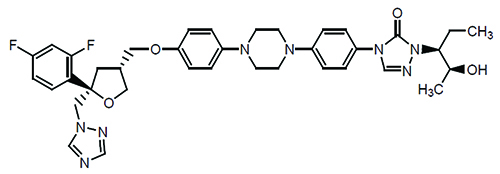 DRUG LABEL: Posaconazole
NDC: 42291-919 | Form: TABLET, DELAYED RELEASE
Manufacturer: AvKARE
Category: prescription | Type: HUMAN PRESCRIPTION DRUG LABEL
Date: 20260119

ACTIVE INGREDIENTS: POSACONAZOLE 100 mg/1 1
INACTIVE INGREDIENTS: SILICON DIOXIDE; CROSCARMELLOSE SODIUM; FERROSOFERRIC OXIDE; HYDROXYPROPYL CELLULOSE, UNSPECIFIED; HYPROMELLOSE ACETATE SUCCINATE 06081224 (3 MM2/S); FERRIC OXIDE YELLOW; POLYETHYLENE GLYCOL, UNSPECIFIED; MAGNESIUM STEARATE; MICROCRYSTALLINE CELLULOSE; POLYVINYL ALCOHOL, UNSPECIFIED; TALC; TITANIUM DIOXIDE

HIGHLIGHTS OF PRESCRIBING INFORMATION

POSACONAZOLE delayed-release tablets, for oral use
These highlights do not include all the information needed to use POSACONAZOLE DELAYED-RELEASE TABLETS safely and effectively. See full prescribing information for POSACONAZOLE DELAYED-RELEASE TABLETS.
Initial U.S. Approval:2006

RECENT MAJOR CHANGES

Contraindications (4) 1/2022
Warnings and Precautions (5) 1/2022

1 INDICATIONS AND USAGE

Posaconazole delayed-release tablets are an azole antifungal indicated as follows:

- Posaconazole delayed-release tablets are indicated for the prophylaxis of invasive Aspergillus and Candida infections in patients who are at high risk of developing these infections due to being severely immunocompromised, such as hematopoietic stem cell transplant (HSCT) recipients with graft-versus-host disease (GVHD) or those with hematologic malignancies with prolonged neutropenia from chemotherapy as follows: (1.2)

- Posaconazole delayed-release tablets: adults and pediatric patients 13 years of age and older

2 DOSAGE AND ADMINISTRATION

- Noxafil® oral suspension is not substitutable with posaconazole delayed-release tablets or Noxafil® PowderMix for delayed-release oral suspension due to the differences in the dosing of each formulation. Therefore, follow the specific dosage recommendations for each of the formulations. (2.1,2.2, 2.3)
- Administer posaconazole delayed-release tablets with or without food. (2.1)

Table 1: Recommended Dosage in Adult Patients and Pediatric Patients aged 13 years and older
Indication | Dosage Form, Dose, and Duration of Therapy
Prophylaxis of invasive Aspergillus and Candida infections | Posaconazole Delayed-Release Tablets:; Loading dose: 300 mg (three 100 mg delayed-release tablets) twice a day on the; first day.; Maintenance dose: 300 mg (three 100 mg delayed-release tablets) once a day, starting on the second day. Duration of therapy is based on recovery from neutropenia or immunosuppression. (2.2)

3 DOSAGE FORMS AND STRENGTHS

- Posaconazole delayed-release tablet: 100 mg (3)

4 CONTRAINDICATIONS

- Known hypersensitivity to posaconazole or other azole antifungal agents. (4.1)
- Co-administration of posaconazole with the following drugs is contraindicated; posaconazole increases concentrations and toxicities of:
- Sirolimus (4.2, 5.1, 7.1)
- CYP3A4 substrates (pimozide, quinidine): can result in QTc interval prolongation and cases of torsades de pointes (TdP) (4.3, 5.2, 7.2)
- HMG-CoA Reductase Inhibitors Primarily Metabolized through CYP3A4 (4.4, 7.3)
- Ergot alkaloids (4.5, 7.4)
- Venetoclax: in patients with chronic lymphocytic leukemia (CLL) or small lymphocytic lymphoma (SLL) at initiation and during the ramp up phase (4.6, 5.10, 7.16)

5 WARNINGS AND PRECAUTIONS

- Calcineurin-Inhibitor Toxicity: Posaconazole increases concentrations of cyclosporine or tacrolimus; reduce dose of cyclosporine and tacrolimus and monitor concentrations frequently. (5.1)
- Arrhythmias and QTc Prolongation: Posaconazole has been shown to prolong the QTc interval and cause cases of TdP. Administer with caution to patients with potentially proarrhythmic conditions. Do not administer with drugs known to prolong QTc interval and metabolized through CYP3A4. (5.2)
- Electrolyte Disturbances: Monitor and correct, especially those involving potassium (K^+), magnesium (Mg^++), and calcium (Ca^++), before and during posaconazole therapy. (5.3)
- Hepatic Toxicity: Elevations in liver tests may occur. Discontinuation should be considered in patients who develop abnormal liver tests or monitor liver tests during treatment. (5.4)
- Concomitant Use with Midazolam: Posaconazole can prolong hypnotic/sedative effects. Monitor patients and benzodiazepine receptor antagonists should be available. (5.6,7.5)
- Vincristine Toxicity: Concomitant administration of azole antifungals, including posaconazole, with vincristine has been associated with neurotoxicity and other serious adverse reactions; reserve azole antifungals, including posaconazole, for patients receiving a vinca alkaloid, including vincristine, who have no alternative antifungal treatment options. (5.7,7.10)
- Breakthrough Fungal Infections: Monitor patients with severe diarrhea or vomiting when receiving posaconazole delayed-release tablets. (5.9)
- Venetoclax Toxicity: Concomitant administration of posaconazole with venetoclax may increase venetoclax toxicities, including the risk of tumor lysis syndrome, neutropenia, and serious infections; monitor for toxicity and reduce venetoclax dose. (4.6, 5.10, 7.16)

6 ADVERSE REACTIONS

- Common adverse reactions in studies with posaconazole are diarrhea, nausea, fever, vomiting, headache, coughing, and hypokalemia. (6.1)

To report SUSPECTED ADVERSE REACTIONS, contact AvKARE 1-855-361-3993 or FDA at 1-800-FDA-1088 or www.fda.gov/medwatch.

7 DRUG INTERACTIONS

Interaction Drug | Interaction
Rifabutin, phenytoin, efavirenz, cimetidine, esomeprazole* | Avoid co-administration unless the benefit outweighs the risks (7.6,7.7,7.8,7.9)
Other drugs metabolized by CYP3A4 | Consider dosage adjustment and monitor for adverse effects and toxicity (7.1,7.10,7.11)
Digoxin | Monitor digoxin plasma concentrations (7.12)
Fosamprenavir, metoclopramide* | Monitor for breakthrough fungal infections (7.6,7.13)
*The drug interactions with esomeprazole and metoclopramide do not apply to posaconazole tablets.

8 USE IN SPECIFIC POPULATIONS

- Pregnancy: Based on animal data, may cause fetal harm. (8.1)
- Pediatrics: Safety and effectiveness in patients younger than 2 years of age have not been established. (8.4)
- Severe Renal Impairment: Monitor closely for breakthrough fungal infections. (8.6)

Additional Pediatric Use information is approved for Merck Sharp & Dohme Corp.’s NOXAFIL (posaconazole) delayed-release tablets. However, due to Merck Sharp & Dohme Corp.’s marketing exclusivity rights, this drug product is not labeled with that pediatric information.

FULL PRESCRIBING INFORMATION

1 INDICATIONS AND USAGE

1.2 Prophylaxis of Invasive Aspergillus and Candida Infections

Posaconazole delayed-release tablets are indicated for the prophylaxis of invasive Aspergillus and Candida infections in patients who are at high risk of developing these infections due to being severely immunocompromised, such as hematopoietic stem cell transplant (HSCT) recipients with graft-versus-host disease (GVHD) or those with hematologic malignancies with prolonged neutropenia from chemotherapy as follows:

- Posaconazole delayed-release tablets: adults and pediatric patients 13 years of age and older

Additional Pediatric Use information is approved for Merck Sharp & Dohme Corp.’s NOXAFIL (posaconazole) delayed-release tablets. However, due to Merck Sharp & Dohme Corp.’s marketing exclusivity rights, this drug product is not labeled with that pediatric information.

2 DOSAGE AND ADMINISTRATION

2.1 Important Administration Instructions

Non-substitutable

Noxafil® oral suspension is not substitutable with posaconazole delayed-release tablets or Noxafil® PowderMix for delayed-release oral suspension due to the differences in the dosing of each formulation. Therefore, follow the specific dosage recommendations for each of the formulations [see Dosage and Administration (2.2, 2.3)] .

Posaconazole delayed-release tablets

- Swallow tablets whole. Do not divide, crush, or chew.
- Administer with or without food [see Dosage and Administration (2.5)and Clinical Pharmacology (12.3)] .
- For patients who cannot eat a full meal, posaconazole delayed-release tablets should be used instead of Noxafil® oral suspension for the prophylaxis indication. Posaconazole delayed-release tablets generally provide higher plasma drug exposures than Noxafil® oral suspension under both fed and fasted conditions, and therefore is the preferred oral formulation for the prophylaxis indication.

2.2 Dosing Regimen in Adult Patients

Table 1: Dosing Regimens in Adult Patients
Indication | Dose and Frequency | Duration of Therapy
Prophylaxis of invasive Aspergillus and Candida infections | Posaconazole Delayed-Release Tablets:; Loading dose: 300 mg (three 100 mg delayed-release tablets) twice a day on the first day.; Maintenance dose: 300 mg (three 100 mg delayed-release tablets) once a day, starting on the second day. | Loading dose:; 1 day; Maintenance dose:; Duration of therapy is based on recovery from neutropenia or immunosuppression.

2.3 Dosing Regimen in Pediatric Patients (ages 13 to less than 18 years of age)

The recommended dosing regimen of posaconazole delayed-release tablets for pediatric patients 13 to less than 18 years of age is shown in Table 2 [see Dosage and Administration (2.5) and Clinical Pharmacology (12.3)] .

Table 2: Posaconazole Delayed-Release Tablet Dosing Regimens for Pediatric Patients (ages 13 to less than 18 years of age)

Recommended Pediatric Dosage and Formulation
Indication |  | Delayed-Release Tablet |  | Duration of therapy
Prophylaxis of invasive Aspergillus and Candida infections |  |  |  | Duration of therapy is based on recovery from neutropenia or immunosuppression.
Prophylaxis of invasive Aspergillus and Candida infections |  | Loading dose:; 300 mg twice daily on the first day; Maintenance dose: 300 mg; once daily |  | Duration of therapy is based on recovery from neutropenia or immunosuppression.

Additional Pediatric Use information is approved for Merck Sharp & Dohme Corp.’s NOXAFIL (posaconazole) delayed-release tablets. However, due to Merck Sharp & Dohme Corp.’s marketing exclusivity rights, this drug product is not labeled with that pediatric information.

2.5 Administration Instructions for Posaconazole Delayed-Release Tablets

- Swallow tablets whole. Do not divide, crush, or chew.
- Administer posaconazole delayed-release tablets with or without food [see Clinical Pharmacology (12.3)] .
- Posaconazole delayed-release tablets should be used only for the prophylaxis indication [see Dosage and Administration (2.1)] .

2.7 Non-substitutability between Noxafil® Oral Suspension and Other Formulations

Noxafil® oral suspension is not substitutable with posaconazole delayed-release tablets due to the differences in the dosing of each formulation. Therefore, follow the specific dosage recommendations for each of the formulations [see Dosage and Administration (2.2, 2.3)] .

2.9 Dosage Adjustments in Patients with Renal Impairment

The pharmacokinetics of posaconazole delayed-release tablets are not significantly affected by renal impairment. Therefore, no adjustment is necessary for oral dosing in patients with mild to severe renal impairment.

3 DOSAGE FORMS AND STRENGTHS

Posaconazole Delayed-Release Tablets

Posaconazole delayed-release tablets are available as yellow, oblong, film coated, unscored tablets, debossed with "AC71" on one side and plain on other side containing 100 mg of posaconazole.

4 CONTRAINDICATIONS

4.1 Hypersensitivity

Posaconazole delayed-release tablets are contraindicated in persons with known hypersensitivity to posaconazole or other azole antifungal agents.

4.2 Use with Sirolimus

Posaconazole is contraindicated with sirolimus. Concomitant administration of posaconazole with sirolimus increases the sirolimus blood concentrations by approximately 9-fold and can result in sirolimus toxicity [see Drug Interactions (7.1)and Clinical Pharmacology (12.3)] .

4.3 QT Prolongation with Concomitant Use with CYP3A4 Substrates

Posaconazole is contraindicated with CYP3A4 substrates that prolong the QT interval. Concomitant administration of posaconazole with the CYP3A4 substrates, pimozide and quinidine may result in increased plasma concentrations of these drugs, leading to QTc prolongation and cases of torsades de pointes [see Warnings and Precautions (5.2)and Drug Interactions (7.2)] .

4.4 HMG-CoA Reductase Inhibitors Primarily Metabolized Through CYP3A4

Co-administration with the HMG-CoA reductase inhibitors that are primarily metabolized through CYP3A4 (e.g., atorvastatin, lovastatin, and simvastatin) is contraindicated since increased plasma concentration of these drugs can lead to rhabdomyolysis [see Drug Interactions (7.3)and Clinical Pharmacology (12.3)] .

4.5 Use with Ergot Alkaloids

Posaconazole may increase the plasma concentrations of ergot alkaloids (ergotamine and dihydroergotamine) which may lead to ergotism [see Drug Interactions (7.4)] .

4.6 Use with Venetoclax

Co-administration of posaconazole with venetoclax at initiation and during the ramp-up phase is contraindicated in patients with chronic lymphocytic leukemia (CLL) or small lymphocytic lymphoma (SLL) due to the potential for increased risk of tumor lysis syndrome [see Warnings and Precautions (5.10) and Drug Interactions (7.16)] .

5 WARNINGS AND PRECAUTIONS

5.1 Calcineurin-Inhibitor Toxicity

Concomitant administration of posaconazole with cyclosporine or tacrolimus increases the whole blood trough concentrations of these calcineurin-inhibitors [see Drug Interactions (7.1)and Clinical Pharmacology (12.3)] . Nephrotoxicity and leukoencephalopathy (including deaths) have been reported in clinical efficacy studies in patients with elevated cyclosporine or tacrolimus concentrations. Frequent monitoring of tacrolimus or cyclosporine whole blood trough concentrations should be performed during and at discontinuation of posaconazole treatment and the tacrolimus or cyclosporine dose adjusted accordingly.

5.2 Arrhythmias and QT Prolongation

Some azoles, including posaconazole, have been associated with prolongation of the QT interval on the electrocardiogram. In addition, cases of torsades de pointes have been reported in patients taking posaconazole.

Results from a multiple time-matched ECG analysis in healthy volunteers did not show any increase in the mean of the QTc interval. Multiple, time-matched ECGs collected over a 12-hour period were recorded at baseline and steady-state from 173 healthy male and female volunteers (18 to 85 years of age) administered Noxafil® oral suspension 400 mg twice daily with a high-fat meal. In this pooled analysis, the mean QTc (Fridericia) interval change from baseline was –5 msec following administration of the recommended clinical dose. A decrease in the QTc(F) interval (–3 msec) was also observed in a small number of subjects (n=16) administered placebo. The placebo-adjusted mean maximum QTc(F) interval change from baseline was <0 msec (–8 msec). No healthy subject administered posaconazole had a QTc(F) interval ≥500 msec or an increase ≥60 msec in their QTc(F) interval from baseline.

Posaconazole should be administered with caution to patients with potentially proarrhythmic conditions. Do not administer with drugs that are known to prolong the QTc interval and are metabolized through CYP3A4 [see Contraindications (4.3)and Drug Interactions (7.2)] .

5.3 Electrolyte Disturbances

Electrolyte disturbances, especially those involving potassium, magnesium or calcium levels, should be monitored and corrected as necessary before and during posaconazole therapy.

5.4 Hepatic Toxicity

Hepatic reactions (e.g., mild to moderate elevations in alanine aminotransferase (ALT), aspartate aminotransferase (AST), alkaline phosphatase, total bilirubin, and/or clinical hepatitis) have been reported in clinical trials. The elevations in liver tests were generally reversible on discontinuation of therapy, and in some instances these tests normalized without drug interruption. Cases of more severe hepatic reactions including cholestasis or hepatic failure including deaths have been reported in patients with serious underlying medical conditions (e.g., hematologic malignancy) during treatment with posaconazole. These severe hepatic reactions were seen primarily in subjects receiving the Noxafil® oral suspension 800 mg daily (400 mg twice daily or 200 mg four times a day) in clinical trials.

Liver tests should be evaluated at the start of and during the course of posaconazole therapy. Patients who develop abnormal liver tests during posaconazole therapy should be monitored for the development of more severe hepatic injury. Patient management should include laboratory evaluation of hepatic function (particularly liver tests and bilirubin). Discontinuation of posaconazole must be considered if clinical signs and symptoms consistent with liver disease develop that may be attributable to posaconazole.

5.5 Renal Impairment

Due to the variability in exposure with posaconazole delayed-release tablets, patients with severe renal impairment should be monitored closely for breakthrough fungal infections [see Dosage and Administration (2.9)and Use in Specific Populations (8.6)] .

5.6 Midazolam Toxicity

Concomitant administration of posaconazole with midazolam increases the midazolam plasma concentrations by approximately 5-fold. Increased plasma midazolam concentrations could potentiate and prolong hypnotic and sedative effects. Patients must be monitored closely for adverse effects associated with high plasma concentrations of midazolam and benzodiazepine receptor antagonists must be available to reverse these effects [see Drug Interactions (7.5)and Clinical Pharmacology (12.3)] .

5.7 Vincristine Toxicity

Concomitant administration of azole antifungals, including posaconazole, with vincristine has been associated with neurotoxicity and other serious adverse reactions, including seizures, peripheral neuropathy, syndrome of inappropriate antidiuretic hormone secretion, and paralytic ileus. Reserve azole antifungals, including posaconazole, for patients receiving a vinca alkaloid, including vincristine, who have no alternative antifungal treatment options [see Drug Interactions (7.10)] .

5.9 Breakthrough Fungal Infections

Patients who have severe diarrhea or vomiting should be monitored closely for breakthrough fungal infections when receiving posaconazole delayed-release tablets.

5.10 Venetoclax Toxicity

Concomitant administration of posaconazole, a strong CYP3A4 inhibitor, with venetoclax may increase venetoclax toxicities, including the risk of tumor lysis syndrome (TLS), neutropenia, and serious infections. In patients with CLL/SLL, administration of posaconazole during initiation and the ramp-up phase of venetoclax is contraindicated [see Contraindications (4.6)] . Refer to the venetoclax labeling for safety monitoring and dose reduction in the steady daily dosing phase in CLL/SLL patients.

For patients with acute myeloid leukemia (AML), dose reduction and safety monitoring are recommended across all dosing phases when co-administering posaconazole with venetoclax [see Drug Interactions (7.16)] . Refer to the venetoclax prescribing information for dosing instructions.

6 ADVERSE REACTIONS

The following serious and otherwise important adverse reactions are discussed in detail in another section of the labeling:

- Hypersensitivity [see Contraindications (4.1)]
- Arrhythmias and QT Prolongation [see Warnings and Precautions (5.2)]
- Hepatic Toxicity [see Warnings and Precautions (5.4)]

6.1 Clinical Trials Experience

Because clinical trials are conducted under widely varying conditions, adverse reaction rates observed in clinical trials of posaconazole cannot be directly compared to rates in the clinical trials of another drug and may not reflect the rates observed in practice.

Clinical Trial Experience in Adults

Clinical Trial Experience with Posaconazole Delayed-Release Tablets for Prophylaxis

The safety of posaconazole delayed-release tablets has been assessed in 230 patients in clinical trials. Patients were enrolled in a non-comparative pharmacokinetic and safety trial of posaconazole delayed-release tablets when given as antifungal prophylaxis (Posaconazole Delayed-Release Tablet Study). Patients were immunocompromised with underlying conditions including hematological malignancy, neutropenia post-chemotherapy, GVHD, and post HSCT. This patient population was 62% male, had a mean age of 51 years (range 19 to 78 years, 17% of patients were ≥65 years of age), and were 93% white and 16% Hispanic. Posaconazole therapy was given for a median duration of 28 days. Twenty patients received 200 mg daily dose and 210 patients received 300 mg daily dose (following twice daily dosing on Day 1 in each cohort). Table 9 presents adverse reactions observed in patients treated with 300 mg daily dose at an incidence of ≥10% in Posaconazole Delayed-Release Tablet Study.

Table 9: Posaconazole Delayed-Release Tablet Study: Adverse Reactions in at Least 10% of Subjects Treated with 300 mg Daily Dose
Body System | Posaconazole delayed-release tablet (300 mg) n=210 (%)
Subjects Reporting any Adverse Reaction | 207 | (99)
Blood and Lymphatic System Disorder
Anemia | 22 | (10)
Thrombocytopenia | 29 | (14)
Gastrointestinal Disorders
Abdominal Pain | 23 | (11)
Constipation | 20 | (10)
Diarrhea | 61 | (29)
Nausea | 56 | (27)
Vomiting | 28 | (13)
General Disorders and Administration Site Conditions
Asthenia | 20 | (10)
Chills | 22 | (10)
Mucosal Inflammation | 29 | (14)
Edema Peripheral | 33 | (16)
Pyrexia | 59 | (28)
Metabolism and Nutrition Disorders
Hypokalemia | 46 | (22)
Hypomagnesemia | 20 | (10)
Nervous System Disorders
Headache | 30 | (14)
Respiratory, Thoracic and Mediastinal Disorders
Cough | 35 | (17)
Epistaxis | 30 | (14)
Skin and Subcutaneous Tissue Disorders
Rash | 34 | (16)
Vascular Disorders
Hypertension | 23 | (11)

The most frequently reported adverse reactions (>25%) with posaconazole delayed-release tablets 300 mg once daily were diarrhea, pyrexia, and nausea.

The most common adverse reaction leading to discontinuation of posaconazole delayed-release tablets 300 mg once daily was nausea (2%).

Additional Pediatric Use information is approved for Merck Sharp & Dohme Corp.’s NOXAFIL (posaconazole) delayed-release tablets. However, due to Merck Sharp & Dohme Corp.’s marketing exclusivity rights, this drug product is not labeled with that pediatric information.

6.2 Postmarketing Experience

The following adverse reaction has been identified during the post-approval use of posaconazole. Because these reactions are reported voluntarily from a population of uncertain size, it is not always possible to reliably estimate their frequency.

Endocrine Disorders: Pseudoaldosteronism

To report SUSPECTED ADVERSE REACTIONS, contact AvKARE 1-855-361-3993 or FDA at 1-800-FDA-1088 or www.fda.gov/medwatch.

7 DRUG INTERACTIONS

Posaconazole is primarily metabolized via UDP glucuronosyltransferase and is a substrate of p-glycoprotein (P-gp) efflux. Therefore, inhibitors or inducers of these clearance pathways may affect posaconazole plasma concentrations. Co-administration of drugs that can decrease the plasma concentrations of posaconazole should generally be avoided unless the benefit outweighs the risk. If such drugs are necessary, patients should be monitored closely for breakthrough fungal infections.

Posaconazole is also a strong inhibitor of CYP3A4. Therefore, plasma concentrations of drugs predominantly metabolized by CYP3A4 may be increased by posaconazole [see Clinical Pharmacology (12.3)] .

The following information was derived from data with Noxafil® oral suspension or early tablet formulation unless otherwise noted. All drug interactions with Noxafil® oral suspension, except for those that affect the absorption of posaconazole (via gastric pH and motility), are considered relevant to Noxafil® injection, posaconazole delayed-release tablet, Noxafil® PowderMix for delayed-release oral suspension as well [see Drug Interactions (7.9)and (7.13)] .

7.1 Immunosuppressants Metabolized by CYP3A4

Sirolimus: Concomitant administration of posaconazole with sirolimus increases the sirolimus blood concentrations by approximately 9-fold and can result in sirolimus toxicity. Therefore, posaconazole is contraindicated with sirolimus [see Contraindications (4.2)and Clinical Pharmacology (12.3)] .

Tacrolimus: Posaconazole has been shown to significantly increase the Cmax and AUC of tacrolimus. At initiation of posaconazole treatment, reduce the tacrolimus dose to approximately one-third of the original dose. Frequent monitoring of tacrolimus whole blood trough concentrations should be performed during and at discontinuation of posaconazole treatment and the tacrolimus dose adjusted accordingly [see Warnings and Precautions (5.1)and Clinical Pharmacology (12.3)] .

Cyclosporine: Posaconazole has been shown to increase cyclosporine whole blood concentrations in heart transplant patients upon initiation of posaconazole treatment. It is recommended to reduce cyclosporine dose to approximately three-fourths of the original dose upon initiation of posaconazole treatment. Frequent monitoring of cyclosporine whole blood trough concentrations should be performed during and at discontinuation of posaconazole treatment and the cyclosporine dose adjusted accordingly [see Warnings and Precautions (5.1)and Clinical Pharmacology (12.3)] .

7.2 CYP3A4 Substrates

Concomitant administration of posaconazole with CYP3A4 substrates such as pimozide and quinidine may result in increased plasma concentrations of these drugs, leading to QTc prolongation and cases of torsades de pointes. Therefore, posaconazole is contraindicated with these drugs [see Contraindications (4.3)and Warnings and Precautions (5.2)] .

7.3 HMG-CoA Reductase Inhibitors (Statins) Primarily Metabolized Through CYP3A4

Concomitant administration of posaconazole with simvastatin increases the simvastatin plasma concentrations by approximately 10-fold. Therefore, posaconazole is contraindicated with HMG-CoA reductase inhibitors primarily metabolized through CYP3A4 [see Contraindications (4.4)and Clinical Pharmacology (12.3)] .

7.4 Ergot Alkaloids

Most of the ergot alkaloids are substrates of CYP3A4. Posaconazole may increase the plasma concentrations of ergot alkaloids (ergotamine and dihydroergotamine) which may lead to ergotism. Therefore, posaconazole is contraindicated with ergot alkaloids [see Contraindications (4.5)] .

7.5 Benzodiazepines Metabolized by CYP3A4

Concomitant administration of posaconazole with midazolam increases the midazolam plasma concentrations by approximately 5-fold. Increased plasma midazolam concentrations could potentiate and prolong hypnotic and sedative effects. Concomitant use of posaconazole and other benzodiazepines metabolized by CYP3A4 (e.g., alprazolam, triazolam) could result in increased plasma concentrations of these benzodiazepines. Patients must be monitored closely for adverse effects associated with high plasma concentrations of benzodiazepines metabolized by CYP3A4 and benzodiazepine receptor antagonists must be available to reverse these effects [see Warnings and Precautions (5.6)and Clinical Pharmacology (12.3)] .

7.6 Anti-HIV Drugs

Efavirenz: Efavirenz induces UDP-glucuronidase and significantly decreases posaconazole plasma concentrations [see Clinical Pharmacology (12.3)] . It is recommended to avoid concomitant use of efavirenz with posaconazole unless the benefit outweighs the risks.

Ritonavir and Atazanavir: Ritonavir and atazanavir are metabolized by CYP3A4 and posaconazole increases plasma concentrations of these drugs [see Clinical Pharmacology (12.3)] . Frequent monitoring of adverse effects and toxicity of ritonavir and atazanavir should be performed during co-administration with posaconazole.

Fosamprenavir: Combining fosamprenavir with posaconazole may lead to decreased posaconazole plasma concentrations. If concomitant administration is required, close monitoring for breakthrough fungal infections is recommended [see Clinical Pharmacology (12.3)] .

7.7 Rifabutin

Rifabutin induces UDP-glucuronidase and decreases posaconazole plasma concentrations. Rifabutin is also metabolized by CYP3A4. Therefore, co-administration of rifabutin with posaconazole increases rifabutin plasma concentrations [see Clinical Pharmacology (12.3)] . Concomitant use of posaconazole and rifabutin should be avoided unless the benefit to the patient outweighs the risk. However, if concomitant administration is required, close monitoring for breakthrough fungal infections as well as frequent monitoring of full blood counts and adverse reactions due to increased rifabutin plasma concentrations (e.g., uveitis, leukopenia) are recommended.

7.8 Phenytoin

Phenytoin induces UDP-glucuronidase and decreases posaconazole plasma concentrations. Phenytoin is also metabolized by CYP3A4. Therefore, co-administration of phenytoin with posaconazole increases phenytoin plasma concentrations [see Clinical Pharmacology (12.3)] . Concomitant use of posaconazole and phenytoin should be avoided unless the benefit to the patient outweighs the risk. However, if concomitant administration is required, close monitoring for breakthrough fungal infections is recommended and frequent monitoring of phenytoin concentrations should be performed while co-administered with posaconazole and dose reduction of phenytoin should be considered.

7.9 Gastric Acid Suppressors/Neutralizers

Posaconazole Delayed-Release Tablet:

No clinically relevant effects on the pharmacokinetics of posaconazole were observed when posaconazole delayed-release tablets are concomitantly used with antacids, H2-receptor antagonists and proton pump inhibitors [see Clinical Pharmacology (12.3)] . No dosage adjustment of posaconazole delayed-release tablets is required when concomitantly used with antacids, H2-receptor antagonists and proton pump inhibitors.

7.10 Vinca Alkaloids

Most of the vinca alkaloids (e.g., vincristine and vinblastine) are substrates of CYP3A4. Concomitant administration of azole antifungals, including posaconazole, with vincristine has been associated with serious adverse reactions [see Warnings and Precautions (5.7)] . Posaconazole may increase the plasma concentrations of vinca alkaloids which may lead to neurotoxicity and other serious adverse reactions. Therefore, reserve azole antifungals, including posaconazole, for patients receiving a vinca alkaloid, including vincristine, who have no alternative antifungal treatment options.

7.11 Calcium Channel Blockers Metabolized by CYP3A4

Posaconazole may increase the plasma concentrations of calcium channel blockers metabolized by CYP3A4 (e.g., verapamil, diltiazem, nifedipine, nicardipine, felodipine). Frequent monitoring for adverse reactions and toxicity related to calcium channel blockers is recommended during co-administration. Dose reduction of calcium channel blockers may be needed.

7.12 Digoxin

Increased plasma concentrations of digoxin have been reported in patients receiving digoxin and posaconazole. Therefore, monitoring of digoxin plasma concentrations is recommended during co-administration.

7.13 Gastrointestinal Motility Agents

Posaconazole Delayed-Release Tablet:

Concomitant administration of metoclopramide with posaconazole delayed-release tablets did not affect the pharmacokinetics of posaconazole [see Clinical Pharmacology (12.3)] . No dosage adjustment of posaconazole delayed-release tablets are required when given concomitantly with metoclopramide.

7.14 Glipizide

Although no dosage adjustment of glipizide is required, it is recommended to monitor glucose concentrations when posaconazole and glipizide are concomitantly used.

7.16 Venetoclax

Concomitant use of venetoclax (a CYP3A4 substrate) with posaconazole increases venetoclax Cmax and AUC0-INF, which may increase venetoclax toxicities [see Contraindications (4.6)and Warnings and Precautions (5.10)] . Refer to the venetoclax prescribing information for more information on the dosing instructions and the extent of increase in venetoclax exposure.

8 USE IN SPECIFIC POPULATIONS

8.1 Pregnancy

Risk Summary

Based on findings from animal data, posaconazole may cause fetal harm when administered to pregnant women. Available data for use of posaconazole in pregnant women are insufficient to establish a drug-associated risk of major birth defects, miscarriage, or adverse maternal or fetal outcomes. In animal reproduction studies, skeletal malformations (cranial malformations and missing ribs) and maternal toxicity (reduced food consumption and reduced body weight gain) were observed when posaconazole was dosed orally to pregnant rats during organogenesis at doses ≥1.4 times the 400 mg twice daily oral suspension regimen based on steady-state plasma concentrations of posaconazole in healthy volunteers. In pregnant rabbits dosed orally during organogenesis, increased resorptions, reduced litter size, and reduced body weight gain of females were seen at doses 5 times the exposure achieved with the 400 mg twice daily oral suspension regimen. Doses of ≥3 times the clinical exposure caused an increase in resorptions in these rabbits (see Data) . Based on animal data, advise pregnant women of the potential risk to a fetus.

The estimated background risk of major birth defects and miscarriage for the indicated population is unknown. All pregnancies have a background risk of birth defect, loss, or other adverse outcomes. In the U.S. general population, the estimated background risk of major birth defects and miscarriage in clinically recognized pregnancies is 2% to 4% and 15% to 20%, respectively.

Data

Animal Data

Posaconazole resulted in maternal toxicity (reduced food consumption and reduced body weight gain) and skeletal malformations (cranial malformations and missing ribs) when given orally to pregnant rats during organogenesis (Gestational Days 6 through 15) at doses ≥27 mg/kg (≥1.4 times the 400 mg twice daily oral suspension regimen based on steady-state plasma concentrations of drug in healthy volunteers). The no-effect dose for malformations and maternal toxicity in rats was 9 mg/kg, which is 0.7 times the exposure achieved with the 400 mg twice daily oral suspension regimen. No malformations were seen in rabbits dosed during organogenesis (Gestational Days 7 through 19) at doses up to 80 mg/kg (5 times the exposure achieved with the 400 mg twice daily oral suspension regimen). In the rabbit, the no-effect dose was 20 mg/kg, while high doses of 40 mg/kg and 80 mg/kg (3 or 5 times the clinical exposure) caused an increase in resorptions. In rabbits dosed at 80 mg/kg, a reduction in body weight gain of females and a reduction in litter size were seen.

8.2 Lactation

Risk Summary

There are no data on the presence of posaconazole in human milk, the effects on the breastfed infant, or the effects on milk production. Posaconazole is excreted in the milk of lactating rats. When a drug is present in animal milk, it is likely that the drug will be present in human milk. The developmental and health benefits of breastfeeding should be considered along with the mother’s clinical need for posaconazole and any potential adverse effects on the breastfed child from posaconazole or from the underlying maternal condition.

8.4 Pediatric Use

The safety and effectiveness of posaconazole delayed-release tablets and Noxafil® oral suspension for the prophylaxis of invasive Aspergillus and Candida infections have been established in pediatric patients aged 13 years and older who are at high risk of developing these infections due to being severely immunocompromised, such as HSCT recipients with GVHD or those with hematologic malignancies with prolonged neutropenia from chemotherapy.

Use of posaconazole in these age groups is supported by evidence from adequate and well-controlled studies of posaconazole in adult and pediatric patients and additional pharmacokinetic and safety data in pediatric patients 13 years of age and older [see Adverse Reactions (6.1), Clinical Pharmacology (12.3)and Clinical Studies (14)] .

The safety and effectiveness of posaconazole have not been established in pediatric patients younger than 2 years of age.

Additional Pediatric Use information is approved for Merck Sharp & Dohme Corp.’s NOXAFIL (posaconazole) delayed-release tablets. However, due to Merck Sharp & Dohme Corp.’s marketing exclusivity rights, this drug product is not labeled with that pediatric information.

8.5 Geriatric Use

No overall differences in the safety of posaconazole delayed-release tablets were observed between geriatric patients and younger adult patients in the clinical trials; therefore, no dosage adjustment is recommended for any formulation of posaconazole in geriatric patients. No clinically meaningful differences in the pharmacokinetics of posaconazole were observed in geriatric patients compared to younger adult patients during clinical trials [see Clinical Pharmacology (12.3)] .

Of the 230 patients treated with posaconazole delayed-release tablets, 38 (17%) were greater than 65 years of age. Of the 288 patients randomized to posaconazole injection/posaconazole delayed-release tablets in the Aspergillosis Treatment Study, 85 (29%) were ≥65 years of age.

No overall differences in the pharmacokinetics and safety were observed between elderly and young subjects during clinical trials, but greater sensitivity of some older individuals cannot be ruled out.

8.6 Renal Impairment

Following single-dose administration of 400 mg of the Noxafil® oral suspension, there was no significant effect of mild (eGFR: 50 to 80 mL/min/1.73 m^2, n=6) or moderate (eGFR: 20 to 49 mL/min/1.73 m^2, n=6) renal impairment on posaconazole pharmacokinetics; therefore, no dose adjustment is required in patients with mild to moderate renal impairment. In subjects with severe renal impairment (eGFR: <20 mL/min/1.73 m^2), the mean plasma exposure (AUC) was similar to that in patients with normal renal function (eGFR: >80 mL/min/1.73 m^2); however, the range of the AUC estimates was highly variable (CV=96%) in these subjects with severe renal impairment as compared to that in the other renal impairment groups (CV<40%). Due to the variability in exposure, patients with severe renal impairment should be monitored closely for breakthrough fungal infections [see Dosage and Administration (2)] . Similar recommendations apply to posaconazole delayed-release tablets; however, a specific study has not been conducted with the delayed-release tablets.

8.7 Hepatic Impairment

After a single oral dose of Noxafil® oral suspension 400 mg, the mean AUC was 43%, 27%, and 21% higher in subjects with mild (Child-Pugh Class A, N=6), moderate (Child-Pugh Class B, N=6), or severe (Child-Pugh Class C, N=6) hepatic impairment, respectively, compared to subjects with normal hepatic function (N=18). Compared to subjects with normal hepatic function, the mean Cmax was 1% higher, 40% higher, and 34% lower in subjects with mild, moderate, or severe hepatic impairment, respectively. The mean apparent oral clearance (CL/F) was reduced by 18%, 36%, and 28% in subjects with mild, moderate, or severe hepatic impairment, respectively, compared to subjects with normal hepatic function. The elimination half-life (t½) was 27 hours, 39 hours, 27 hours, and 43 hours in subjects with normal hepatic function and mild, moderate, or severe hepatic impairment, respectively.

It is recommended that no dose adjustment of posaconazole delayed-release tablets is needed in patients with mild to severe hepatic impairment (Child-Pugh Class A, B, or C) [see Dosage and Administration (2)and Warnings and Precautions (5.4)] . However, a specific study has not been conducted with posaconazole delayed-release tablets.

8.8 Gender

The pharmacokinetics of posaconazole are comparable in males and females. No adjustment in the dosage of posaconazole is necessary based on gender.

8.9 Race

The pharmacokinetic profile of posaconazole is not significantly affected by race. No adjustment in the dosage of posaconazole is necessary based on race.

8.10 Weight

Pharmacokinetic modeling suggests that patients weighing greater than 120 kg may have lower posaconazole plasma drug exposure. It is, therefore, suggested to closely monitor for breakthrough fungal infections.

10 OVERDOSAGE

There is no experience with overdosage of posaconazole delayed-release tablets.

During the clinical trials, some patients received Noxafil® oral suspension up to 1,600 mg/day with no adverse reactions noted that were different from the lower doses. In addition, accidental overdose was noted in one patient who took 1,200 mg twice daily Noxafil® oral suspension for 3 days. No related adverse reactions were noted by the investigator.

Posaconazole is not removed by hemodialysis.

11 DESCRIPTION

Posaconazole is an azole antifungal agent. Posaconazole is available as a delayed-release tablet.

Posaconazole is designated chemically as 4-[4-[4-[4-[[ (3 R,5 R)-5- (2,4-difluorophenyl)tetrahydro-5- (1 H-1,2,4-triazol-1-ylmethyl)-3-furanyl]methoxy]phenyl]-1-piperazinyl]phenyl]-2-[(1 S,2 S)-1-ethyl-2-hydroxypropyl]-2,4-dihydro-3 H-1,2,4-triazol-3-one with an empirical formula of C37H42F2N8O4 and a molecular weight of 700.8. The chemical structure is:

Posaconazole is a white powder with a low aqueous solubility.

Posaconazole Delayed-Release Tablets

Posaconazole delayed-release tablets are yellow, oblong, film coated, unscored tablets containing 100 mg of posaconazole. Each delayed-release tablet contains the inactive ingredients: colloidal silicon dioxide, croscarmellose sodium, ferrosoferric oxide black, hydroxypropylcellulose, hypromellose acetate succinate, iron oxide yellow, Macrogol/PEG 3350, magnesium stearate, microcrystalline cellulose, polyvinyl alcohol partially hydrolyzed, talc and titanium dioxide.

12 CLINICAL PHARMACOLOGY

12.1 Mechanism of Action

Posaconazole is an azole antifungal agent [see Clinical Pharmacology (12.4)] .

12.2 Pharmacodynamics

Exposure Response Relationship Prophylaxis: In clinical studies of neutropenic patients who were receiving cytotoxic chemotherapy for acute myelogenous leukemia (AML) or myelodysplastic syndromes (MDS) or hematopoietic stem cell transplant (HSCT) recipients with Graft versus Host Disease (GVHD), a wide range of plasma exposures to posaconazole was noted following administration of Noxafil® oral suspension. A pharmacokinetic-pharmacodynamic analysis of patient data revealed an apparent association between average posaconazole concentrations (Cavg) and prophylactic efficacy (Table 17). A lower Cavg may be associated with an increased risk of treatment failure, defined as treatment discontinuation, use of empiric systemic antifungal therapy (SAF), or occurrence of breakthrough invasive fungal infections.

Table 17: Noxafil® Oral Suspension Exposure Analysis (Cavg) in Prophylaxis Trials
 | Prophylaxis in AML/MDS* |  | Prophylaxis in GVHD†
 | Cavg Range (ng/mL) | Treatment Failure‡ (%) | Cavg Range (ng/mL) | Treatment Failure‡ (%)
Quartile 1 | 90 to 322 | 54.7 | 22 to 557 | 44.4
Quartile 2 | 322 to 490 | 37.0 | 557 to 915 | 20.6
Quartile 3 | 490 to 734 | 46.8 | 915 to 1563 | 17.5
Quartile 4 | 734 to 2200 | 27.8 | 1,563 to 3650 | 17.5
Cavg = the average posaconazole concentration when measured at steady-state
* Neutropenic patients who were receiving cytotoxic chemotherapy for AML or MDS
† HSCT recipients with GVHD
‡ Defined as treatment discontinuation, use of empiric systemic antifungal therapy (SAF), or occurrence of breakthrough invasive fungal infections

12.3 Pharmacokinetics

General Pharmacokinetic Characteristics

Posaconazole Delayed-Release Tablets

Posaconazole delayed-release tablets exhibit dose proportional pharmacokinetics after single and multiple dosing up to 300 mg. The mean pharmacokinetic parameters of posaconazole at steady-state following administration of posaconazole delayed-release tablets 300 mg twice daily on Day 1, then 300 mg once daily thereafter in healthy volunteers and in neutropenic patients who are receiving cytotoxic chemotherapy for AML or MDS or HSCT recipients with GVHD are shown in Table 20.

Table 20: Arithmetic Mean (%CV) of Steady-State PK Parameters in Healthy Volunteers and Patients Following Administration of Posaconazole Delayed-Release Tablets (300 mg)*
 | N | AUC0-24 hr (ng·hr/mL) | Cav† (ng/mL) | Cmax (ng/mL) | Cmin (ng/mL) | Tmax‡ (hr) | t1/2 (hr) | CL/F (L/hr)
Healthy Volunteers | 12 | 51,618 (25) | 2,151 (25) | 2,764 (21) | 1,785 (29) | 4 (3 to 6) | 31 (40) | 7.5 (26)
Patients | 50 | 37,900 (42) | 1,580 (42) | 2,090 (38) | 1,310 (50) | 4 (1.3 to 8.3) | - | 9.39 (45)
CV = coefficient of variation expressed as a percentage (%CV); AUC0-T = Area under the plasma concentration-time curve from time zero to 24 hr; Cmax = maximum observed concentration; Cmin = minimum observed plasma concentration; Tmax = time of maximum observed concentration; t½ = terminal phase half-life; CL/F = Apparent total body clearance
*300 mg twice daily on Day 1, then 300 mg once daily thereafter
† Cav = time-averaged concentrations (i.e., AUC0-24 hr/24hr)
‡ Median (minimum-maximum)

Absorption:

Posaconazole Delayed-Release Tablets

When given orally in healthy volunteers, posaconazole delayed-release tablets are absorbed with a median Tmax of 4 to 5 hours. Steady-state plasma concentrations are attained by Day 6 at the 300 mg dose (once daily after twice daily loading dose at Day 1). The absolute bioavailability of the oral delayed-release tablet is approximately 54% under fasted conditions. The Cmax and AUC of posaconazole following administration of posaconazole delayed-release tablets is increased 16% and 51%, respectively, when given with a high fat meal compared to a fasted state (see Table 22).

Table 22: Statistical Comparison of Plasma Pharmacokinetics of Posaconazole Following Single Oral Dose Administration of 300 mg Posaconazole Delayed-Release Tablet to Healthy Subjects under Fasting and Fed Conditions
 | Fasting Conditions |  | Fed Conditions (High Fat Meal)* |  | Fed/Fasting
Pharmacokinetic Parameter | N | Mean (%CV) | N | Mean (%CV) | GMR (90% CI)
Cmax (ng/mL) | 14 | 935 (34) | 16 | 1,060 (25) | 1.16 (0.96, 1.41)
AUC0-72hr (hr∙ng/mL) | 14 | 26,200 (28) | 16 | 38,400 (18) | 1.51 (1.33, 1.72)
Tmax† (hr) | 14 | 5.00 (3.00, 8.00) | 16 | 6.00 (5.00, 24.00) | N/A
GMR=Geometric least-squares mean ratio; CI=Confidence interval
* 48.5 g fat
† Median (Min, Max) reported for Tmax

Concomitant administration of posaconazole delayed-release tablets with drugs affecting gastric pH or gastric motility did not demonstrate any significant effects on posaconazole pharmacokinetic exposure (see Table 23).

Table 23: The Effect of Concomitant Medications that Affect the Gastric pH and Gastric Motility on the Pharmacokinetics of Posaconazole Delayed-Release Tablets in Healthy Volunteers
Co-administered Drug | Administration Arms | Change in Cmax (ratio estimate*; 90% CI of the ratio estimate) | Change in AUC0-last (ratio estimate*; 90% CI of the ratio estimate)
Mylanta® Ultimate strength liquid (Increase in gastric pH) | 25.4 meq/5 mL, 20 mL | ↑6% (1.06; 0.90 to 1.26)↑ | ↑4% (1.04; 0.90 to 1.20)
Ranitidine (Zantac®) (Alteration in gastric pH) | 150 mg (morning dose of 150 mg Ranitidine twice daily) | ↑4% (1.04; 0.88 to 1.23)↑ | ↓3% (0.97; 0.84 to 1.12)
Esomeprazole (Nexium®) (Increase in gastric pH) | 40 mg (every morning for 5 days, Day -4 to 1) | ↑2% (1.02; 0.88 to 1.17)↑ | ↑5% (1.05; 0.89 to 1.24)
Metoclopramide (Reglan®) (Increase in gastric motility) | 15 mg four times daily for 2 days (Day -1 and 1) | ↓14% (0.86, 0.73,1.02) | ↓7% (0.93, 0.803,1.07)
* Ratio Estimate is the ratio of co-administered drug plus posaconazole to posaconazole alone for Cmax or AUC0-last.

Distribution:

The mean volume of distribution of posaconazole after intravenous solution administration was 261 L and ranged from 226 to 295 L between studies and dose levels.

Posaconazole is highly bound to human plasma proteins (>98%), predominantly to albumin.

Metabolism:

Posaconazole primarily circulates as the parent compound in plasma. Of the circulating metabolites, the majority are glucuronide conjugates formed via UDP glucuronidation (phase 2 enzymes). Posaconazole does not have any major circulating oxidative (CYP450 mediated) metabolites. The excreted metabolites in urine and feces account for ~17% of the administered radiolabeled dose.

Posaconazole is primarily metabolized via UDP glucuronidation (phase 2 enzymes) and is a substrate for p-glycoprotein (P-gp) efflux. Therefore, inhibitors or inducers of these clearance pathways may affect posaconazole plasma concentrations. A summary of drugs studied clinically with the oral suspension or an early tablet formulation, which affect posaconazole concentrations, is provided in Table 27.

Table 27: Summary of the Effect of Co-administered Drugs on Posaconazole in Healthy Volunteers
Co-administered Drug (Postulated Mechanism of Interaction) | Co-administered Drug Dose/Schedule | Posaconazole Dose/Schedule | Effect on Bioavailability of Posaconazole
Co-administered Drug (Postulated Mechanism of Interaction) | Co-administered Drug Dose/Schedule | Posaconazole Dose/Schedule | Change in Mean Cmax (ratio estimate*; 90% CI of the ratio estimate) | Change in Mean AUC (ratio estimate*; 90% CI of the ratio estimate)
Efavirenz (UDP-G Induction) | 400 mg once daily × 10 and 20 days | 400 mg (oral suspension) twice daily × 10 and 20 days | ↓45% (0.55; 0.47 to 0.66) | ↓ 50% (0.50; 0.43 to 0.60)
Fosamprenavir (unknown mechanism) | 700 mg twice daily × 10 days | 200 mg once daily on the 1st day, 200 mg twice daily on the 2nd day, then 400 mg twice daily × 8 Days | ↓21% 0.79 (0.71 to 0.89) | ↓23% 0.77 (0.68 to 0.87)
Rifabutin (UDP-G Induction) | 300 mg once daily × 17 days | 200 mg (tablets) once daily × 10 days† | ↓ 43% (0.57; 0.43 to 0.75) | ↓ 49% (0.51; 0.37 to 0.71)
Phenytoin (UDP-G Induction) | 200 mg once daily × 10 days | 200 mg (tablets) once daily × 10 days† | ↓ 41% (0.59; 0.44 to 0.79) | ↓ 50% (0.50; 0.36 to 0.71)
* Ratio Estimate is the ratio of co-administered drug plus posaconazole to posaconazole alone for Cmax or AUC.
† The tablet refers to a non-commercial tablet formulation without polymer.

In vitro studies with human hepatic microsomes and clinical studies indicate that posaconazole is an inhibitor primarily of CYP3A4. A clinical study in healthy volunteers also indicates that posaconazole is a strong CYP3A4 inhibitor as evidenced by a >5-fold increase in midazolam AUC. Therefore, plasma concentrations of drugs predominantly metabolized by CYP3A4 may be increased by posaconazole. A summary of the drugs studied clinically, for which plasma concentrations were affected by posaconazole, is provided in Table 28 [see Contraindications (4)and Drug Interactions (7.1) including recommendations] .

Table 28: Summary of the Effect of Posaconazole on Co-administered Drugs in Healthy Adult Volunteers and Patients
Co-administered Drug (Postulated Mechanism of Interaction is Inhibition of CYP3A4 by posaconazole) | Co-administered Drug Dose/Schedule | Posaconazole Dose/Schedule | Effect on Bioavailability of Co-administered Drugs
Co-administered Drug (Postulated Mechanism of Interaction is Inhibition of CYP3A4 by posaconazole) | Co-administered Drug Dose/Schedule | Posaconazole Dose/Schedule | Change in Mean Cmax (ratio estimate*; 90% CI of the ratio estimate) | Change in Mean AUC (ratio estimate*; 90% CI of the ratio estimate)
Sirolimus | 2-mg single oral dose | 400 mg (oral suspension) twice daily × 16 days | ↑ 572% (6.72; 5.62 to 8.03) | ↑ 788% (8.88; 7.26 to 10.9)
Cyclosporine | Stable maintenance dose in heart transplant recipients | 200 mg (tablets) once daily × 10 days† | ↑ cyclosporine whole blood trough concentrations Cyclosporine dose reductions of up to 29% were required
Tacrolimus | 0.05-mg/kg single oral dose | 400 mg (oral suspension) twice daily × 7 days | ↑ 121% (2.21; 2.01 to 2.42) | ↑ 358% (4.58; 4.03 to 5.19)
Simvastatin | 40-mg single oral dose | 100 mg (oral suspension) once daily × 13 days | Simvastatin ↑ 841% (9.41, 7.13 to 12.44); Simvastatin Acid ↑ 817% (9.17, 7.36 to 11.43) | Simvastatin ↑ 931% (10.31, 8.40 to 12.67); Simvastatin Acid ↑634% (7.34, 5.82 to 9.25)
Simvastatin | 40-mg single oral dose | 200 mg (oral suspension) once daily × 13 days | Simvastatin ↑ 1041% (11.41, 7.99 to 16.29); Simvastatin Acid ↑851% (9.51, 8.15 to 11.10) | Simvastatin ↑ 960% (10.60, 8.63 to 13.02); Simvastatin Acid ↑748% (8.48, 7.04 to 10.23)
Midazolam | 0.4-mg single intravenous dose‡ | 200 mg (oral suspension) twice daily × 7 days | ↑ 30% (1.3; 1.13 to 1.48) | ↑ 362% (4.62; 4.02 to 5.3)
Midazolam | 0.4-mg single intravenous dose‡ | 400 mg (oral suspension) twice daily × 7 days | ↑62% (1.62; 1.41 to 1.86) | ↑524% (6.24; 5.43 to 7.16)
Midazolam | 2-mg single oral dose‡ | 200 mg (oral suspension) once daily × 7 days | ↑ 169% (2.69; 2.46 to 2.93) | ↑ 470% (5.70; 4.82 to 6.74)
Midazolam | 2-mg single oral dose‡ | 400 mg (oral suspension) twice daily × 7 days | ↑ 138% (2.38; 2.13 to 2.66) | ↑ 397% (4.97; 4.46 to 5.54)
Rifabutin | 300 mg once daily × 17 days | 200 mg (tablets) once daily × 10 days† | ↑ 31% (1.31; 1.10 to 1.57) | ↑ 72% (1.72; 1.51 to 1.95)
Phenytoin | 200 mg once daily PO × 10 days | 200 mg (tablets) once daily × 10 days† | ↑ 16% (1.16; 0.85 to 1.57) | ↑ 16% (1.16; 0.84 to 1.59)
Ritonavir | 100 mg once daily × 14 days | 400 mg (oral suspension) twice daily × 7 days | ↑ 49% (1.49; 1.04 to 2.15) | ↑ 80% (1.8; 1.39 to 2.31)
Atazanavir | 300 mg once daily × 14 days | 400 mg (oral suspension) twice daily × 7 days | ↑ 155% (2.55; 1.89 to 3.45) | ↑ 268% (3.68; 2.89 to 4.70)
Atazanavir/ritonavir boosted regimen | 300 mg/100 mg once daily × 14 days | 400 mg (oral suspension) twice daily × 7 days | ↑ 53% (1.53; 1.13 to 2.07) | ↑ 146% (2.46; 1.93 to 3.13)
* Ratio Estimate is the ratio of co-administered drug plus posaconazole to co-administered drug alone for Cmax or AUC.
† The tablet refers to a non-commercial tablet formulation without polymer.
‡ The mean terminal half-life of midazolam was increased from 3 hours to 7 to 11 hours during co-administration with posaconazole.

Additional clinical studies demonstrated that no clinically significant effects on zidovudine, lamivudine, indinavir, or caffeine were observed when administered with posaconazole 200 mg once daily; therefore, no dose adjustments are required for these co-administered drugs when co-administered with posaconazole 200 mg once daily.

Excretion:

Following administration of Noxafil® Oral suspension, posaconazole is predominantly eliminated in the feces (71% of the radiolabeled dose up to 120 hours) with the major component eliminated as parent drug (66% of the radiolabeled dose). Renal clearance is a minor elimination pathway, with 13% of the radiolabeled dose excreted in urine up to 120 hours (<0.2% of the radiolabeled dose is parent drug).

Posaconazole delayed-release tablet is eliminated with a mean half-life (t½) ranging between 26 to 31 hours.

Specific Populations

No clinically significant differences in the pharmacokinetics of posaconazole were observed based on age, sex, renal impairment, and indication.

Race/Ethnicity:

In a population pharmacokinetic analysis of posaconazole, AUC was found to be 25% higher in Chinese patients relative to patients from other races/ethnicities. This higher exposure is not expected to be clinically relevant given the expected variability in posaconazole exposure.

Patients Weighing More Than 120 kg:

Weight has a clinically significant effect on posaconazole clearance. Relative to 70 kg patients, the Cavg is decreased by 25% in patients greater than 120 kg. Patients administered posaconazole weighing more than 120 kg may be at higher risk for lower posaconazole plasma concentrations compared to lower weight patients [see Use in Specific Populations (8.10)] .

Pediatric Patients

A total of 12 patients 13 to 17 years of age received 600 mg/day (200 mg three times a day) of Noxafil® oral suspension for prophylaxis of invasive fungal infections. Based on pharmacokinetic data in 10 of these pediatric patients, the mean steady-state Cav was similar between these patients and adults (≥18 years of age). In a study of 136 neutropenic pediatric patients 11 months to less than 18 years treated with Noxafil® oral suspension, the exposure target of steady-state posaconazole Cavg between 500 ng/mL and less than 2500 ng/mL was attained in approximately 50% of patients instead of the prespecified 90% of patients .

Additional Pediatric Use information is approved for Merck Sharp & Dohme Corp.’s NOXAFIL (posaconazole) delayed-release tablets. However, due to Merck Sharp & Dohme Corp.’s marketing exclusivity rights, this drug product is not labeled with that pediatric information.

12.4 Microbiology

Mechanism of Action:

Posaconazole blocks the synthesis of ergosterol, a key component of the fungal cell membrane, through the inhibition of cytochrome P-450 dependent enzyme lanosterol 14α-demethylase responsible for the conversion of lanosterol to ergosterol in the fungal cell membrane. This results in an accumulation of methylated sterol precursors and a depletion of ergosterol within the cell membrane thus weakening the structure and function of the fungal cell membrane. This may be responsible for the antifungal activity of posaconazole.

Resistance:

Clinical isolates of Candida albicans and Candida glabrata with decreased susceptibility to posaconazole were observed in oral swish samples taken during prophylaxis with posaconazole and fluconazole, suggesting a potential for development of resistance. These isolates also showed reduced susceptibility to other azoles, suggesting cross-resistance between azoles. The clinical significance of this finding is not known.

Antimicrobial Activity:

Posaconazole has been shown to be active against most isolates of the following microorganisms, both in vitro and in clinical infections [see Indications and Usage (1)] .

Microorganisms:

Aspergillus spp. and Candida spp.

Susceptibility Testing:

For specific information regarding susceptibility test interpretive criteria and associated test methods and quality control standards recognized by FDA for this drug, please see:

https://www.fda.gov/STIC.

13 NONCLINICAL TOXICOLOGY

13.1 Carcinogenesis, Mutagenesis, Impairment of Fertility

Carcinogenesis

No drug-related neoplasms were recorded in rats or mice treated with posaconazole for 2 years at doses higher than the clinical dose. In a 2-year carcinogenicity study, rats were given posaconazole orally at doses up to 20 mg/kg (females), or 30 mg/kg (males). These doses are equivalent to 3.9- or 3.5-times the exposure achieved with a 400-mg twice daily oral suspension regimen, respectively, based on steady-state AUC in healthy volunteers administered a high-fat meal (400-mg twice daily oral suspension regimen). In the mouse study, mice were treated at oral doses up to 60 mg/kg/day or 4.8-times the exposure achieved with a 400-mg twice daily oral suspension regimen.

Mutagenesis

Posaconazole was not genotoxic or clastogenic when evaluated in bacterial mutagenicity (Ames), a chromosome aberration study in human peripheral blood lymphocytes, a Chinese hamster ovary cell mutagenicity study, and a mouse bone marrow micronucleus study.

Impairment of Fertility

Posaconazole had no effect on fertility of male rats at a dose up to 180 mg/kg (1.7 x the 400-mg twice daily oral suspension regimen based on steady-state plasma concentrations in healthy volunteers) or female rats at a dose up to 45 mg/kg (2.2 x the 400-mg twice daily oral suspension regimen).

13.2 Animal Toxicology and/or Pharmacology

In a nonclinical study using intravenous administration of posaconazole in very young dogs (dosed from 2 to 8 weeks of age), an increase in the incidence of brain ventricle enlargement was observed in treated animals as compared with concurrent control animals. No difference in the incidence of brain ventricle enlargement between control and treated animals was observed following the subsequent 5-month treatment-free period. There were no neurologic, behavioral or developmental abnormalities in the dogs with this finding, and a similar brain finding was not seen with oral posaconazole administration to juvenile dogs (4 days to 9 months of age). There were no drug-related increases in the incidence of brain ventricle enlargement when treated and control animals were compared in a separate study of 10-week old dogs dosed with intravenous posaconazole for 13 weeks with a 9-week recovery period or a follow-up study of 31-week old dogs dosed for 3 months.

14 CLINICAL STUDIES

14.2 Prophylaxis of Aspergillus and Candida Infections with Noxafil® Oral Suspension

Two randomized, controlled studies were conducted using posaconazole as prophylaxis for the prevention of invasive fungal infections (IFIs) among patients at high risk due to severely compromised immune systems.

The first study (Noxafil® Oral Suspension Study 1) was a randomized, double-blind trial that compared Noxafil® Oral suspension (200 mg three times a day) with fluconazole capsules (400 mg once daily) as prophylaxis against invasive fungal infections in allogeneic hematopoietic stem cell transplant (HSCT) recipients with Graft versus Host Disease (GVHD). Efficacy of prophylaxis was evaluated using a composite endpoint of proven/probable IFIs, death, or treatment with systemic antifungal therapy (patients may have met more than one of these criteria). This assessed all patients while on study therapy plus 7 days and at 16 weeks post-randomization. The mean duration of therapy was comparable between the 2 treatment groups (80 days, Noxafil® Oral suspension; 77 days, fluconazole). Table 32 contains the results from Noxafil® Oral Suspension Study 1.

Table 32: Results from Blinded Clinical Study in Prophylaxis of IFI in All Randomized Patients with Hematopoietic Stem Cell Transplant (HSCT) and Graft-vs.-Host Disease (GVHD): Noxafil® Oral Suspension Study 1
 | Posaconazole n=301 | Fluconazole n=299
On therapy plus 7 days
Clinical Failure* | 50 (17%) | 55 (18%)
Failure due to:
Proven/Probable IFI | 7 (2%) | 22 (7%)
(Aspergillus) | 3 (1%) | 17 (6%)
(Candida) | 1 (<1%) | 3 (1%)
(Other) | 3 (1%) | 2 (1%)
All Deaths | 22 (7%) | 24 (8%)
Proven/probable fungal infection prior to death | 2 (<1%) | 6 (2%)
SAF† | 27 (9%) | 25 (8%)
Through 16 weeks
Clinical Failure*,‡ | 99 (33%) | 110 (37%)
Failure due to:
Proven/Probable IFI | 16 (5%) | 27 (9%)
(Aspergillus) | 7 (2%) | 21 (7%)
(Candida) | 4 (1%) | 4 (1%)
(Other) | 5 (2%) | 2 (1%)
All Deaths | 58 (19%) | 59 (20%)
Proven/probable fungal infection prior to death | 10 (3%) | 16 (5%)
SAF† | 26 (9%) | 30 (10%)
Event free lost to follow-up§ | 24 (8%) | 30 (10%)
* Patients may have met more than one criterion defining failure.
† Use of systemic antifungal therapy (SAF) criterion is based on protocol definitions (empiric/IFI usage >4 consecutive days).
‡ 95% confidence interval (posaconazole-fluconazole) = (-11.5%, +3.7%).
§ Patients who are lost to follow-up (not observed for 112 days), and who did not meet another clinical failure endpoint. These patients were considered failures.

The second study (Noxafil® Oral Suspension Study 2) was a randomized, open-label study that compared Noxafil® Oral suspension (200 mg 3 times a day) with fluconazole suspension (400 mg once daily) or itraconazole oral solution (200 mg twice a day) as prophylaxis against IFIs in neutropenic patients who were receiving cytotoxic chemotherapy for AML or MDS. As in Noxafil® Oral Suspension Study 1, efficacy of prophylaxis was evaluated using a composite endpoint of proven/probable IFIs, death, or treatment with systemic antifungal therapy (Patients might have met more than one of these criteria). This study assessed patients while on treatment plus 7 days and 100 days post randomization. The mean duration of therapy was comparable between the 2 treatment groups (29 days, posaconazole; 25 days, fluconazole or itraconazole). Table 33 contains the results from Noxafil® Oral Suspension Study 2.

Table 33: Results from Open-Label Clinical Study 2 in Prophylaxis of IFI in All Randomized Patients with Hematologic Malignancy and Prolonged Neutropenia: Noxafil® Oral Suspension Study 2
 | Posaconazole n=304 | Fluconazole/Itraconazole n=298
On therapy plus 7 days
Clinical Failure*,† | 82 (27%) | 126 (42%)
Failure due to:
Proven/Probable IFI | 7 (2%) | 25 (8%)
(Aspergillus) | 2 (1%) | 20 (7%)
(Candida) | 3 (1%) | 2 (1%)
(Other) | 2 (1%) | 3 (1%)
All Deaths | 17 (6%) | 25 (8%)
Proven/probable fungal infection prior to death | 1 (<1%) | 2 (1%)
SAF‡ | 67 (22%) | 98 (33%)
Through 100 days postrandomization
Clinical Failure† | 158 (52%) | 191 (64%)
Failure due to:
Proven/Probable IFI | 14 (5%) | 33 (11%)
(Aspergillus) | 2 (1%) | 26 (9%)
(Candida) | 10 (3%) | 4 (1%)
(Other) | 2 (1%) | 3 (1%)
All Deaths | 44 (14%) | 64 (21%)
Proven/probable fungal infection prior to death | 2 (1%) | 16 (5%)
SAF‡ | 98 (32%) | 125 (42%)
Event free lost to follow-up§ | 34 (11%) | 24 (8%)
* 95% confidence interval (posaconazole-fluconazole/itraconazole) = (-22.9%, -7.8%).
† Patients may have met more than one criterion defining failure.
‡ Use of systemic antifungal therapy (SAF) criterion is based on protocol definitions (empiric/IFI usage >3 consecutive days).
§ Patients who are lost to follow-up (not observed for 100 days), and who did not meet another clinical failure endpoint. These patients were considered failures.

In summary, 2 clinical studies of prophylaxis were conducted with the Noxafil® Oral suspension. As seen in the accompanying tables (Tables 32 and 33), clinical failure represented a composite endpoint of breakthrough IFI, mortality and use of systemic antifungal therapy. In Noxafil® Oral Suspension Study 1 (Table 32), the clinical failure rate of posaconazole (33%) was similar to fluconazole (37%), (95% CI for the difference posaconazole–comparator -11.5% to 3.7%) while in Noxafil® Oral Suspension Study 2 (Table 33) clinical failure was lower for patients treated with posaconazole (27%) when compared to patients treated with fluconazole or itraconazole (42%), (95% CI for the difference posaconazole–comparator -22.9% to -7.8%).

All-cause mortality was similar at 16 weeks for both treatment arms in Noxafil® Oral Suspension Study 1 [POS 58/301 (19%) vs. FLU 59/299 (20%)]; all-cause mortality was lower at 100 days for posaconazole-treated patients in Noxafil® Oral Suspension Study 2 [POS 44/304 (14%) vs. FLU/ITZ 64/298 (21%)]. Both studies demonstrated fewer breakthrough infections caused by Aspergillus species in patients receiving posaconazole prophylaxis when compared to patients receiving fluconazole or itraconazole.

16 HOW SUPPLIED/STORAGE AND HANDLING

16.1 How Supplied

Posaconazole Delayed-Release Tablets

Posaconazole delayed-release tablets 100 mg are available as yellow, oblong, film coated, unscored tablets, debossed with "AC71" on one side and plain on other side. They are supplied as follows:

Bottles of 60 with child-resistant closure: NDC 42291-919-60

16.2 Storage and Handling

Posaconazole Delayed-Release Tablets

Store at 20° to 25°C (68° to 77°F), excursions permitted between 15° to 30°C (59° to 86°F) [see USP Controlled Room Temperature].

17 PATIENT COUNSELING INFORMATION

Advise the patient to read the FDA-approved patient labeling (Patient Information and Instructions for Use).

Important Administration Instructions

Posaconazole Delayed-Release Tablets

Advise patients that posaconazole delayed-release tablets must be swallowed whole and not divided, crushed, or chewed.

Instruct patients that if they miss a dose, they should take it as soon as they remember. If they do not remember until it is within 12 hours of the next dose, they should be instructed to skip the missed dose and go back to the regular schedule. Patients should not double their next dose or take more than the prescribed dose.

Drug Interactions

Advise patients to inform their physician immediately if they:

- develop severe diarrhea or vomiting.
- are currently taking drugs that are known to prolong the QTc interval and are metabolized through CYP3A4.
- are currently taking a cyclosporine or tacrolimus, or they notice swelling in an arm or leg or shortness of breath.
- are taking other drugs or before they begin taking other drugs as certain drugs can decrease or increase the plasma concentrations of posaconazole.

Serious and Potentially Serious Adverse Reactions

Advise patients to inform their physician immediately if they:

- notice a change in heart rate or heart rhythm or have a heart condition or circulatory disease. Posaconazole can be administered with caution to patients with potentially proarrhythmic conditions.
- are pregnant, plan to become pregnant, or are nursing.
- have liver disease or develop itching, nausea or vomiting, their eyes or skin turn yellow, they feel more tired than usual or feel like they have the flu.
- have ever had an allergic reaction to other antifungal medicines such as ketoconazole, fluconazole, itraconazole, or voriconazole.

The trademarks referenced herein are owned by their respective companies.

Manufactured for:

AvKARE

Pulaski, TN 38478

Mfg. Rev. 09-2022-01

AV 01/23 (W)

Patient Information

Posaconazole (poe”sa kon’a zole) Delayed-Release Tablets

What are posaconazole delayed-release tablets?

Posaconazole delayed-release tablets is a prescription medicine used in adults and children 13 years of age and older to help prevent fungal infections that can spread throughout your body (invasive fungal infections). These infections are caused by fungi called Aspergillus or Candida. Posaconazole delayed-release tablets are used in people who have an increased chance of getting these infections due to a weak immune system. These include people who have had a hematopoietic stem cell transplantation (bone marrow transplant) with graft versus host disease or those with a low white blood cell count due to chemotherapy for blood cancers (hematologic malignancies).

Posaconazole delayed-release tablets are used for:

- prevention of fungal infections in patients 13 years of age and older.

It is not known if posaconazole delayed-release tablets are safe and effective in children under 2 years of age.

Who should not take posaconazole delayed-release tablets?

Do not take posaconazole delayed-release tablets if you:

- are allergic to posaconazole, any of the ingredients in posaconazole delayed-release tablets, or other azole antifungal medicines. See the end of this leaflet for a complete list of ingredients in posaconazole delayed-release tablets.
- are taking any of the following medicines:

- sirolimus
- pimozide
- quinidine
- certain statin medicines that lower cholesterol (atorvastatin, lovastatin, simvastatin)
- ergot alkaloids (ergotamine, dihydroergotamine)

- have chronic lymphocytic leukemia (CLL) or small lymphocytic lymphoma (SLL) and you have just started taking venetoclax or your venetoclax dose is being slowly increased.

Ask your healthcare provider or pharmacist if you are not sure if you are taking any of these medicines.

Do not start taking a new medicine without talking to your healthcare provider or pharmacist.

What should I tell my healthcare provider before taking posaconazole delayed-release tablets?

Before you take posaconazole delayed-release tablets, tell your healthcare provider if you:

- are taking certain medicines that lower your immune system like cyclosporine or tacrolimus.
- are taking certain drugs for HIV infection, such as ritonavir, atazanavir, efavirenz, or fosamprenavir. Efavirenz and fosamprenavir can cause a decrease in the posaconazole levels in your body. Efavirenz and fosamprenavir should not be taken with posaconazole delayed-release tablets.
- are taking midazolam, a hypnotic and sedative medicine.
- are taking vincristine, vinblastine and other “vinca alkaloids” (medicines used to treat cancer).
- are taking venetoclax, a medicine used to treat cancer.
- have or had liver problems.
- have or had kidney problems.
- have or had an abnormal heart rate or rhythm, heart problems, or blood circulation problems.
- are pregnant or plan to become pregnant. It is not known if posaconazole delayed-release tablets will harm your unborn baby.
- are breastfeeding or plan to breastfeed. It is not known if posaconazole passes into your breast milk. You and your healthcare provider should decide if you will take posaconazole delayed-release tablets or breastfeed. You should not do both.

Tell your healthcare provider about all the medicines you take, including prescription and over-the-counter medicines, vitamins, and herbal supplements. Posaconazole delayed-release tablets can affect the way other medicines work, and other medicines can affect the way posaconazole delayed-release tablets work, and can cause serious side effects.

Especially tell your healthcare provider if you take:

- rifabutin or phenytoin. If you are taking these medicines, you should not take posaconazole delayed-release tablets.

Ask your healthcare provider or pharmacist for a list of these medicines if you are not sure.

Know the medicines you take. Keep a list of them with you to show your healthcare provider or pharmacist when you get a new medicine.

How will I take posaconazole delayed-release tablets?

- Do not switch between Noxafil® oral suspension and posaconazole delayed-release tablets or Noxafil® PowderMix for delayed-release oral suspension.
- Take posaconazole delayed-release tablets exactly as your healthcare provider tells you to take it.
- Your healthcare provider will tell you how much posaconazole delayed-release tablets to take and when to take it.
- Take posaconazole delayed-release tablets for as long as your healthcare provider tells you to take it.
- If you take too much posaconazole delayed-release tablets, call your healthcare provider or go to the nearest hospital emergency room right away.
- Posaconazole delayed-release tablets:

- Take posaconazole delayed-release tablets with or without food.
- Take posaconazole delayed-release tablets whole. Do not break, crush, or chew posaconazole delayed-release tablets before swallowing. If you cannot swallow posaconazole delayed-release tablets whole, tell your healthcare provider. You may need a different medicine.
- If you miss a dose, take it as soon as you remember and then take your next scheduled dose at its regular time. If it is within 12 hours of your next dose, do not take the missed dose. Skip the missed dose and go back to your regular schedule. Do not double your next dose or take more than your prescribed dose.

Follow the instructions from your healthcare provider on how much posaconazole delayed-release tablets you should take and when to take it.

What are the possible side effects of posaconazole delayed-release tablets?

Posaconazole delayed-release tablets may cause serious side effects, including:

- drug interactions with cyclosporine or tacrolimus. If you take posaconazole delayed-release tablets with cyclosporine or tacrolimus, your blood levels of cyclosporine or tacrolimus may increase. Serious side effects can happen in your kidney or brain if you have high levels of cyclosporine or tacrolimus in your blood. Your healthcare provider should do blood tests to check your levels of cyclosporine or tacrolimus if you are taking these medicines while taking posaconazole delayed-release tablets. Tell your healthcare provider right away if you have swelling in your arm or leg or shortness of breath.
- problems with the electrical system of your heart (arrhythmias and QTc prolongation). Certain medicines used to treat fungus called azoles, including posaconazole, the active ingredient in posaconazole delayed-release tablets, may cause heart rhythm problems. People who have certain heart problems or who take certain medicines have a higher chance for this problem. Tell your healthcare provider right away if your heartbeat becomes fast or irregular.
- Changes in body salt (elecrolytes) levels in your blood. Your healthcare provider should check your electrolytes while you are taking Posaconazole delayed-release tablets.
- liver problems. Some people who also have other serious medical problems may have severe liver problems that may lead to death, especially if you take certain doses of posaconazole delayed-release tablets. Your healthcare provider should do blood tests to check your liver while you are taking posaconazole delayed-release tablets. Call your healthcare provider right away if you have any of the following symptoms of liver problems:

- itchy skin
- nausea or vomiting
- yellowing of your eyes or skin

- feeling very tired
- flu-like symptoms

- increased amounts of midazolam in your blood. If you take posaconazole delayed-release tablets with midazolam, posaconazole delayed-release tablets increases the amount of midazolam in your blood. This can make your sleepiness last longer. Your healthcare provider should check you closely for side effects if you take midazolam with posaconazole delayed-release tablets.

The most common side effects of posaconazole delayed-release tablets include:

- diarrhea
- nausea
- fever
- vomiting

- headache
- coughing
- low potassium levels in the blood

If you take posaconazole delayed-release tablets, tell your healthcare provider right away if you have diarrhea or vomiting.

Tell your healthcare provider if you have any side effect that bothers you or that does not go away.

These are not all the possible side effects of posaconazole delayed-release tablets. For more information, ask your healthcare provider or pharmacist.

Call your doctor for medical advice about side effects. You may report side effects to FDA at 1-800-FDA-1088.

How should I store posaconazole delayed-release tablets?

Posaconazole delayed-release tablets

- Store posaconazole delayed-release tablets at room temperature between 68°F to 77°F (20°C to 25°C).

Safely throw away medicine that is out of date or no longer needed.

Keep posaconazole delayed-release tablets and all medicines out of the reach of children.

General information about the safe and effective use of posaconazole delayed-release tablets.

Medicines are sometimes prescribed for purposes other than those listed in a Patient Information leaflet. Do not use posaconazole delayed-release tablets for a condition for which it was not prescribed. Do not give posaconazole delayed-release tablets to other people, even if they have the same symptoms that you have. It may harm them. You can ask your pharmacist or healthcare provider for information about posaconazole delayed-release tablets that is written for health professionals.

What are the ingredients in posaconazole delayed-release tablets?

Active ingredient: posaconazole

Inactive ingredients:

Posaconazole delayed-release tablets: colloidal silicon dioxide, croscarmellose sodium, ferrosoferric oxide black, hydroxypropylcellulose, hypromellose acetate succinate, iron oxide yellow, Macrogol/PEG 3350, magnesium stearate, microcrystalline cellulose, polyvinyl alcohol partially hydrolyzed, talc, and titanium dioxide.

Additional Pediatric Use information is approved for Merck Sharp & Dohme Corp.’s NOXAFIL (posaconazole) delayed-release tablets. However, due to Merck Sharp & Dohme Corp.’s marketing exclusivity rights, this drug product is not labeled with that pediatric information.

The trademarks depicted in this piece are owned by their respective companies.

Manufactured for:

AvKARE

Pulaski, TN 38478

Mfg. Rev. 09-2022-01

AV 01/23 (W)

For more information, go to www.avkare.com or call 1-855-361-3993.

This Patient Information has been approved by the U.S. Food and Drug Administration.

Rev. 09-2022-01